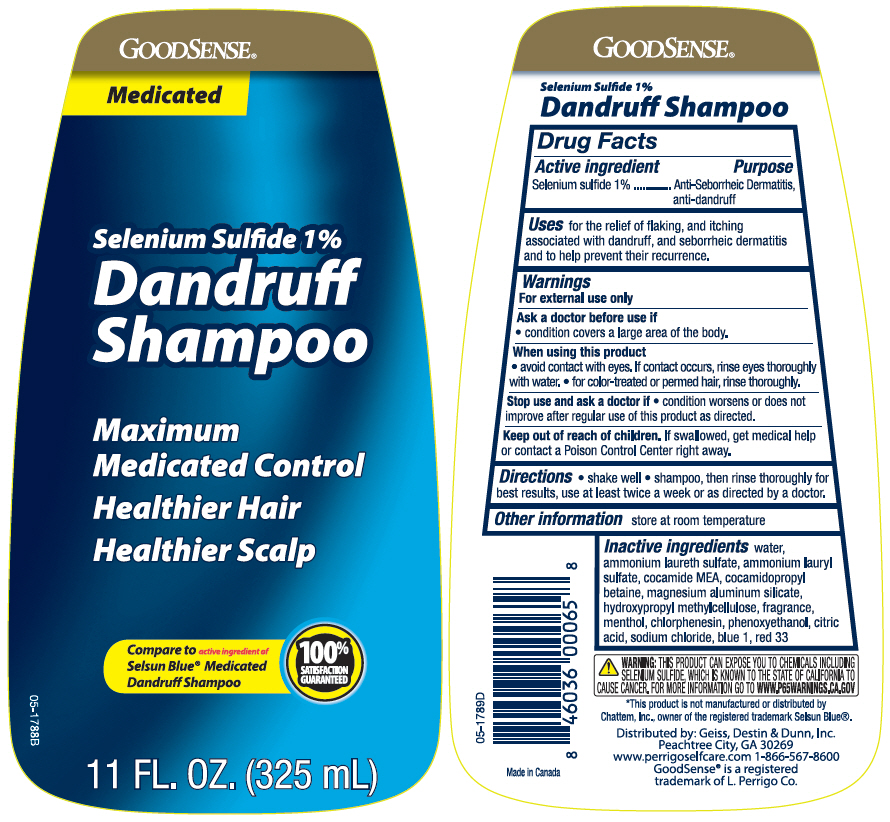 DRUG LABEL: GoodSense Medicated Dandruff
NDC: 50804-883 | Form: SHAMPOO
Manufacturer: GOODSENSE
Category: otc | Type: HUMAN OTC DRUG LABEL
Date: 20200630

ACTIVE INGREDIENTS: Selenium Sulfide 10 mg/1 mL
INACTIVE INGREDIENTS: Water; AMMONIUM LAURETH-5 SULFATE; Ammonium Lauryl Sulfate; COCO MONOETHANOLAMIDE; Cocamidopropyl Betaine; Magnesium Aluminum Silicate; HYPROMELLOSE, UNSPECIFIED; MENTHOL, UNSPECIFIED FORM; Chlorphenesin; Phenoxyethanol; CITRIC ACID MONOHYDRATE; Sodium Chloride; FD&C BLUE NO. 1; D&C RED NO. 33

GoodSense® Medicated Dandruff Shampoo
Anti-Seborrheic Dermatitis, Anti-Dandruff

Drug Facts

Active ingredient

Selenium Sulfide 1%

Purpose

Anti-seborrheic dermatitis, anti-dandruff

Uses

for the relief of flaking, and itching associated with dandruff, and seborrheic dermatitis and to help prevent their recurrence.

Warnings

For external use only

Ask a doctor before use if

- condition covers a large area of the body.

When using this product

- avoid contact with the eyes. If contact occurs, rinse eyes thoroughly with water.
- for color-treated or permed hair, rinse thoroughly.

Stop use and ask a doctor if

- condition worsens or does not improve after regular use of this product as directed.

Keep out of reach of children. If swallowed, get medical help or contact a Poison Control Center right away.

Directions

- shake well
- shampoo, then rinse thoroughly for best results, use at least twice a week or as directed by a doctor.

Other information

store at room temperature

Inactive ingredients

water, ammonium laureth sulfate, ammonium lauryl sulfate, cocamide MEA, cocamidopropyl betaine, magnesium aluminum silicate, hydroxypropyl methylcellulose, fragrance, menthol, chlorphenesin, phenoxyethanol, citric acid, sodium chloride, blue 1, red 33

Distributed by: Geiss, Destin & Dunn, Inc.
Peachtree City, GA 30269

PRINCIPAL DISPLAY PANEL - 325 mL Bottle Label

GOODSENSE®

Medicated

Selenium Sulfide 1%
Dandruff
Shampoo

Maximum
Medicated Control
Healthier Hair
Healthier Scalp

Compare to active ingredient of
Selsun Blue® Medicated
Dandruff Shampoo
100%
SATISFACTION
GUARANTEED

11 FL. OZ. (325 mL)

05-1788B